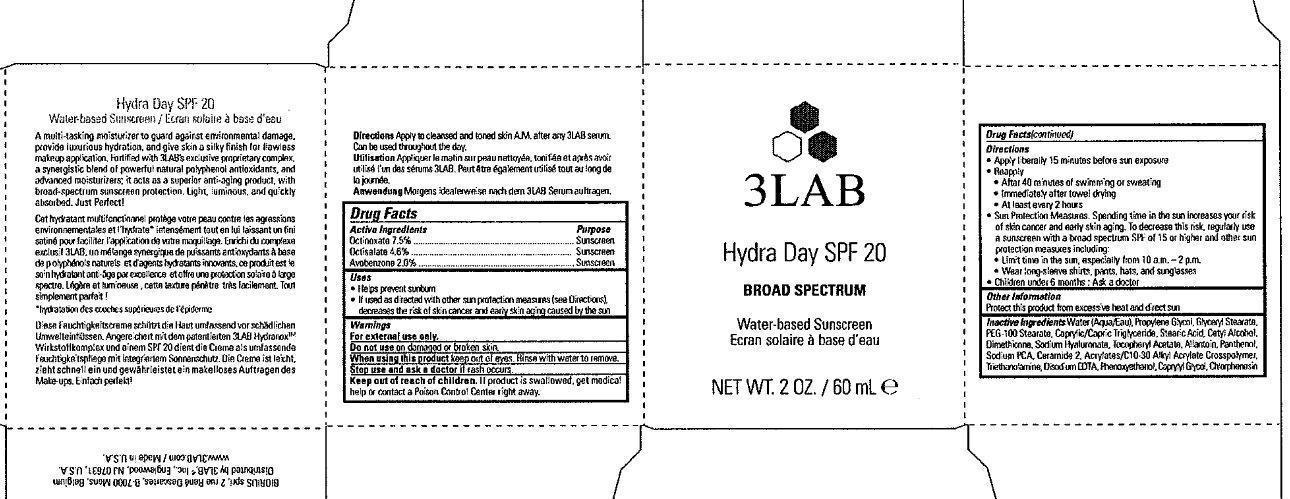 DRUG LABEL: 3LAB Hydra Day SPF 20 Broad Spectrum Water-Based Sunscreen

NDC: 76159-124 | Form: CREAM
Manufacturer: 3LAB, Inc
Category: otc | Type: HUMAN OTC DRUG LABEL
Date: 20231212

ACTIVE INGREDIENTS: OCTINOXATE 75 mg/1 mL; OCTISALATE 46 mg/1 mL; AVOBENZONE 2 mg/1 mL
INACTIVE INGREDIENTS: PEG-100 STEARATE; MEDIUM-CHAIN TRIGLYCERIDES; STEARIC ACID; CETYL ALCOHOL; DIMETHICONE; HYALURONATE SODIUM; .ALPHA.-TOCOPHEROL ACETATE; ALLANTOIN; PANTHENOL; SODIUM PYRROLIDONE CARBOXYLATE; CERAMIDE 2; TROLAMINE; EDETATE DISODIUM; PHENOXYETHANOL; CAPRYLYL GLYCOL; CHLORPHENESIN; WATER; PROPYLENE GLYCOL; GLYCERYL MONOSTEARATE

3LAB Hydra Day SPF 20 Broad Spectrum Water-Based Sunscreen

Active Ingredients

Octinoxate 7.5% Octisalate 4.6% Avobenzone 2.0%

Purpose

Sunscreen

Uses

- Helps prevent sunburn
- If used as directed with other sun protection measures (see Directions), decreases the risk of skin cancer and early skin aging caused by the sun

Warnings

For external use only.

Do not use

on damaged or broken skin.

When using this product

keep out of eyes. Rinse with water to remove.

Stop use and ask a doctor

if rash occurs.

Keep out of reach of children.

If product is swallowed, get medical help or contact a Poison Control Center right away.

Directions

- Apply liberally 15 minutes before sun exposure
- Reapply
- After 40 minutes of swimming or sweating
- Immediately after towel drying
- At least every 2 hours
- Sun Protection Measures. Spending time in the sun increases your risk of skin cancer and early skin aging. To decrease this risk, regularly use a sunscreen with a broad spectrum SPF of 15 or higher and other sun protection measures including:
- Limit time in the sun, especially from 10 a.m. - 2 p.m.
- Wear long-sleeve shirts, pants, hats and sunglasses
- Children under 6 months: Ask a doctor

Other Information

Protect this product from excessive heat and direct sun

Inactive Ingredients

Water (Aqua/Eau), Propylene Glycol, Glyceryl Sterate, PEG-100 Stearate, Caprylic/Capric triglyceride, STearic Acid, Cetyl Alcohol, Dimethicone, Sodium Hyaluronate, Tocopheryl Acetate, Allantoin, Panthenol, Sodium PCA, Ceramide 2, Acrylates/C-10-30 Alkyl Acrylate Crosspolymer, Triethanolamine, Disodium EDTA, Phenoxyethanol, Caprylyl Glycol, Chlorphenesin

Hydra Day SPF 20

Water-based Sunscreen

A multi-tasking moisturizer to guard against environmental damage. Provide luxurious hydration, and give skin a silky finish for flawless makeup application. Fortified with 3LAB's exclusive proprietary complex. a synergistic blend of powerful natural polyphenol antioxidants, and advanced moisturizers: it acts as a superior anti-aging product, with broad-spectrum sunscreen protection. Light, luminous and quickly absorbed. Just Perfect!

PACKAGE LABEL

3LAB Hydra Day SPF 20 BROAD SPECTRUM Water-based Sunscreen NET WT. 2 OZ. / 60 mL e